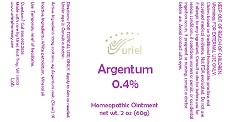 DRUG LABEL: Argentum 0.4
NDC: 48951-1074 | Form: OINTMENT
Manufacturer: Uriel Pharmacy Inc.
Category: homeopathic | Type: HUMAN OTC DRUG LABEL
Date: 20181012

ACTIVE INGREDIENTS: SILVER 1 [hp_X]/1 g
INACTIVE INGREDIENTS: PETROLATUM; MINERAL OIL

Argentum 0.4

INDICATIONS AND USAGE

Directions: FOR TOPICAL USE ONLY.

DOSAGE AND ADMINISTRATION

Apply to skin as needed. Under age 2: Consult a doctor.

Active Ingredient: 100g contains: 4g Argentum met. (Silver) 1X

Inactive Ingredients: White petrolatum, Mineral oil

PURPOSE

Use: Temporary relief of headache.

KEEP OUT OF REACH OF CHILDREN.

Warnings: FOR EXTERNAL USE ONLY.
Claims based on traditional homeopathic practice, not accepted medical evidence. Not FDA evaluated. Do not use if allergic to any ingredient. Consult a doctor before use for serious conditions, if conditions worsen or persist, or accidental ingestion occurs. If pregnant or nursing, consult a doctor before use. Avoid contact with eyes.

QUESTIONS

Questions? Call 866.642.2858 Made with care by Uriel, East Troy, WI 53120 www.urielpharmacy.com